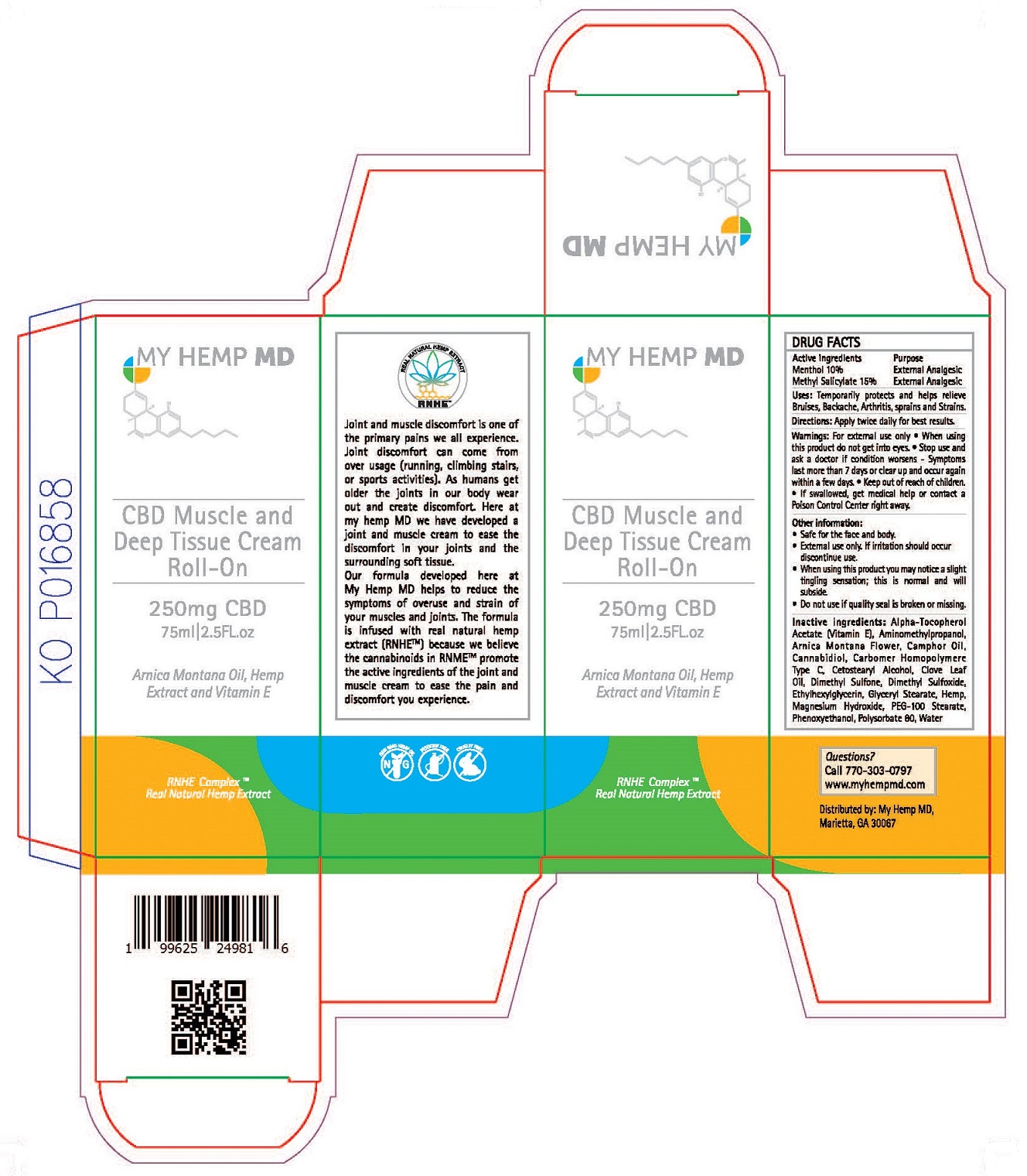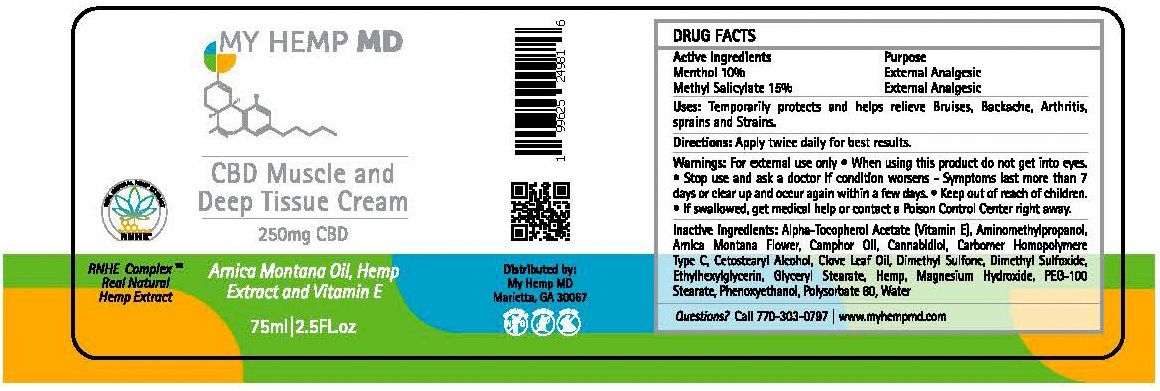 DRUG LABEL: My Hemp MD CBD Muscle and Deep Tissue Cream
NDC: 52261-5202 | Form: CREAM
Manufacturer: Cosco International, Inc.
Category: otc | Type: HUMAN OTC DRUG LABEL
Date: 20200326

ACTIVE INGREDIENTS: MENTHOL 0.10 kg/1 kg; METHYL SALICYLATE 0.15 kg/1 kg
INACTIVE INGREDIENTS: WATER; DIMETHYL SULFONE; CARBOMER HOMOPOLYMER TYPE C; DIMETHYL SULFOXIDE; GLYCERYL MONOSTEARATE; POLYSORBATE 80; ARNICA MONTANA FLOWER; HEMP; CANNABIDIOL; .ALPHA.-TOCOPHEROL ACETATE; GLYCERYL STEARATE/PEG-100 STEARATE; CAMPHOR OIL; CLOVE LEAF OIL; PHENOXYETHANOL; ETHYLHEXYLGLYCERIN; MAGNESIUM HYDROXIDE; AMINOMETHYLPROPANOL

Drug Facts

Active Ingredients....................Purpose

Menthol 5%................................External Analgesic

Methyl Salicylate 10%..................External Analgesic

PURPOSE

External Analgesic

INDICATIONS AND USAGE

Uses: Temporarily helps relieve minor aches and pains of muscle and joints associated with simple backaches, arthritis, sprains, bruises and strains.

Warnings

For external use only

When using tthis product:

- Do not get into eyes.

Stop use and ask a doctor if:

- Condition worsens
- Symptoms last more than 7 days or clear up and occur again within a few days.

Keep out of reach of children:

- If swallowed, get medical help or contact a Poison Control Center right away.

Directions:

Apply twice daily for best results.

Other information:

- External use only. If irratation should occur discontinue use.
- When using this product you may notice a slight tingling sensation; this is normal and will subside.
- Do not use if quality seal is broken or missing.

Inactive ingredients:

Alpha-Tocopherol Acetate (Vitamin E), Aminomethylpropanol, Arnica Montana Flower, Camphor Oil, Cannabidiol, Carbomer Homopolymere Type C, Cetostearyl Alcohol, Clove Leaf Oil, Dimethyl Sulfone, Dimethyl Sulfoxide, Ethylhexylglycerin, Glyceryl Stearate/PEG-100 Stearate, Hemp, Magnesium Hydroxide, Phenoxyethanol, Polysorbate 80, Water

Questions?

Call 770-303-0797

www.myhempmd.com

Distributed by: My Hemp MD

Marietta, GA 30067